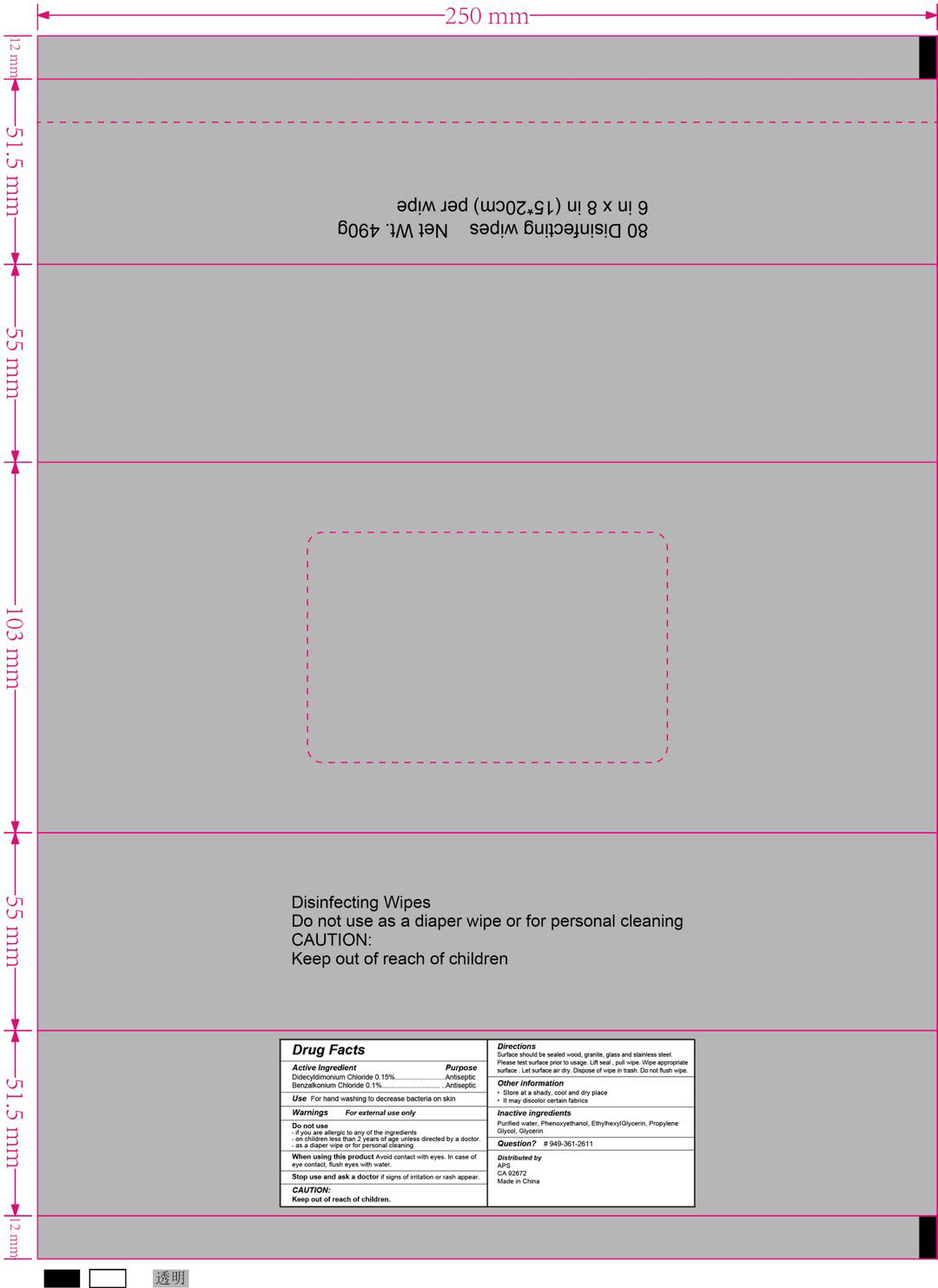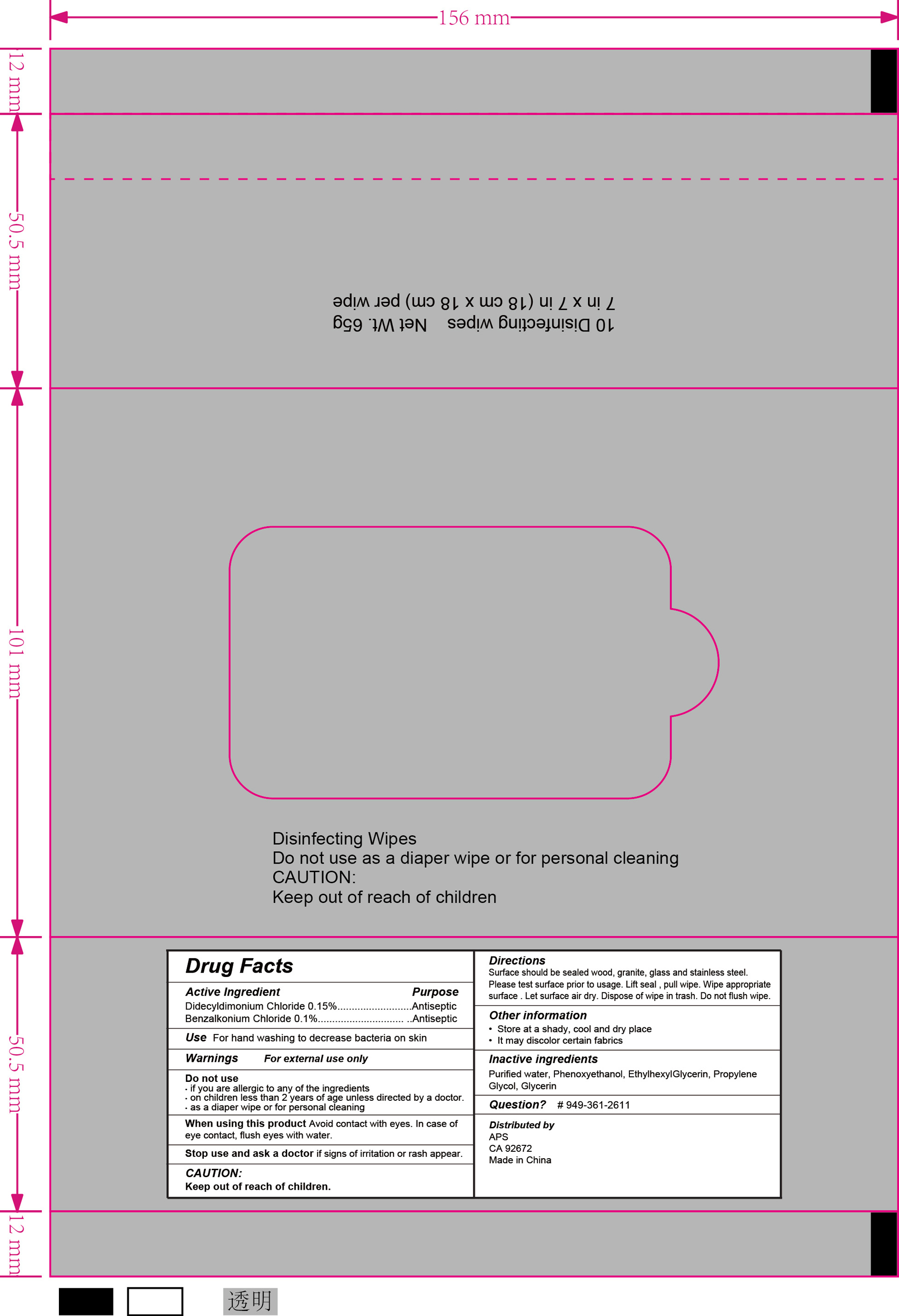 DRUG LABEL: WET WIPES
NDC: 75662-001 | Form: CLOTH
Manufacturer: Ningbo Chenxing Daily Necessities Co., Ltd.
Category: otc | Type: HUMAN OTC DRUG LABEL
Date: 20200502

ACTIVE INGREDIENTS: DIDECYLDIMONIUM CHLORIDE 0.15 g/1 1; BENZALKONIUM CHLORIDE 0.1 g/1 1
INACTIVE INGREDIENTS: ETHYLHEXYLGLYCERIN; PROPYLENE GLYCOL; GLYCERIN; PHENOXYETHANOL; WATER

WET WIPES

Active Ingredient(s)

Didecyldimonium Chloride 0.15%. Purpose: Antiseptic

Benzalkonium Chloride 0.1%. Purpose: Antiseptic

Purpose

Antiseptic, Wet Wipes

Use

For hand washing to decrease bacteria on skin

Warnings

External use only.

Do not use

- if you are allergic to any of the ingredients.
- on children less than 2 years of age unless directed by a doctor.
- as a diaper wipe or for personal cleaning

WHEN USING

Avoid direct contact with eyes. In case of eye contact, flush eyes with water.

Stop use and ask a doctor if signs of irritation or rash appear.

Keep out of reach of children.

Directions

Surface should be sealed wood, granite, glass and stainless steel. Please test surface prior to usage. Lift seal, pull wipe. Wipe appropriate surface. Let surface air dry. Dispose of wipe in trash. Do not flush wipe.

Other information

- Store at a shady, cool and dry place
- It may discolor certain fabrics

Inactive ingredients

Purified water, Phenoxyethanol, Ethylhexyl Glycerin, Propylene Glycol, Glycerin

RECENT MAJOR CHANGES

Indications and Usage

Dosage and Administration

Package Label - Principal Display Panel

75662-001-01 80 wipes

75662-001-02 10 wipes